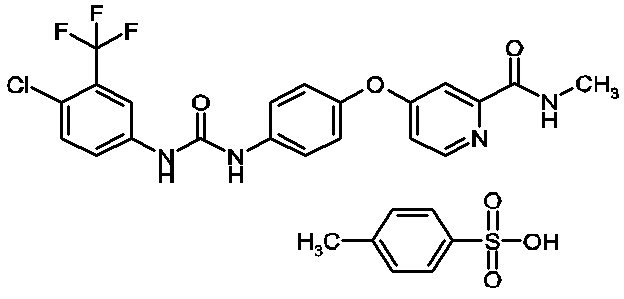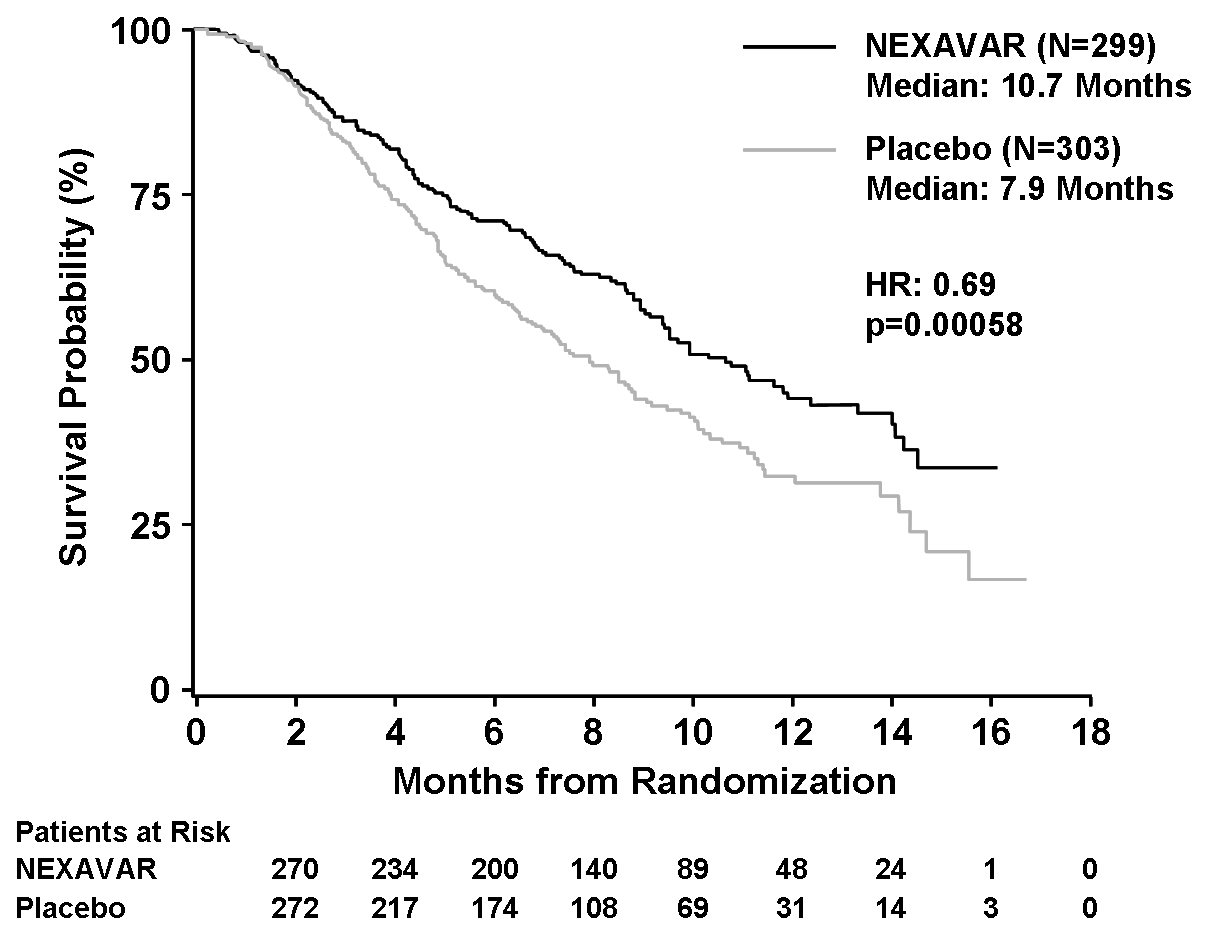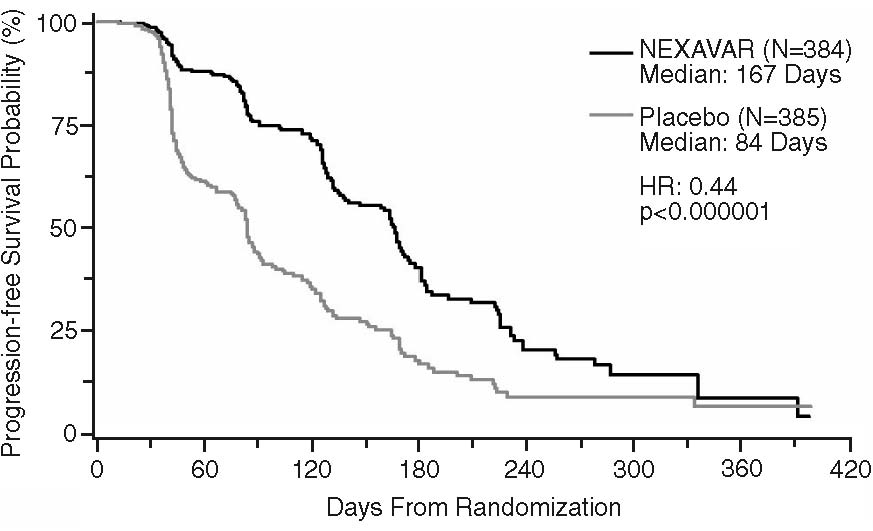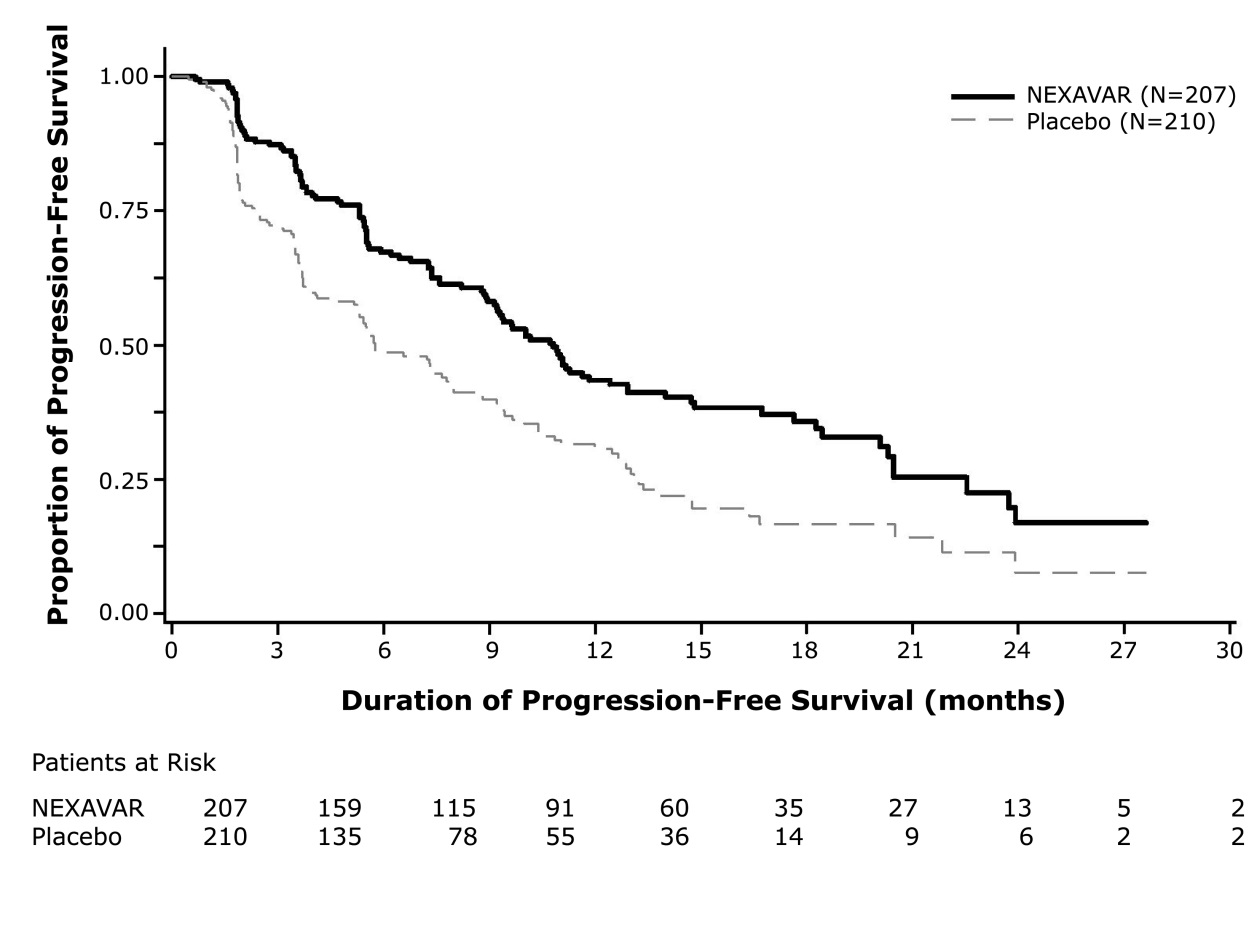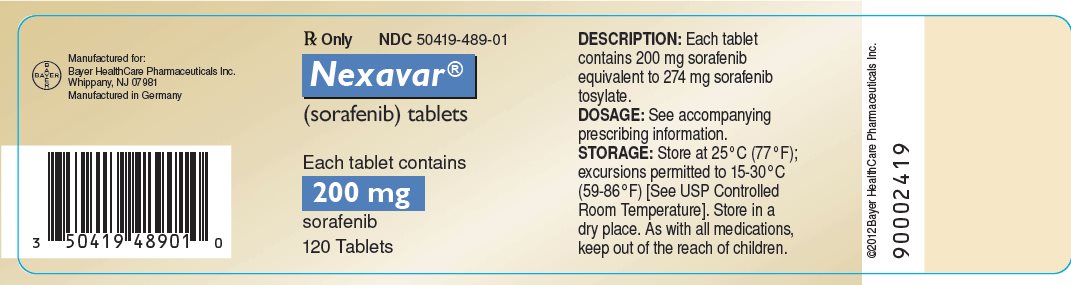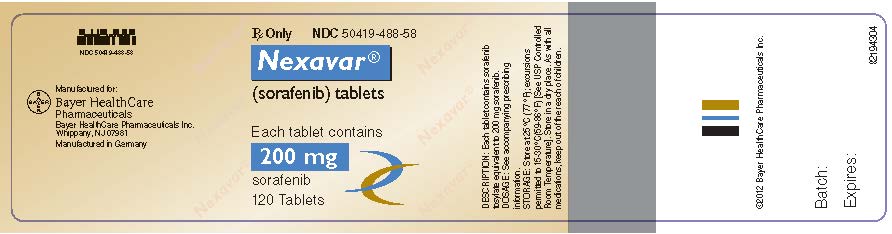 DRUG LABEL: Nexavar
NDC: 50419-488 | Form: TABLET, FILM COATED
Manufacturer: Bayer HealthCare Pharmaceuticals Inc.
Category: prescription | Type: HUMAN PRESCRIPTION DRUG LABEL
Date: 20230828

ACTIVE INGREDIENTS: SORAFENIB 200 mg/1 1
INACTIVE INGREDIENTS: CROSCARMELLOSE SODIUM; MICROCRYSTALLINE CELLULOSE; HYPROMELLOSE, UNSPECIFIED; SODIUM LAURYL SULFATE; MAGNESIUM STEARATE; POLYETHYLENE GLYCOL, UNSPECIFIED; TITANIUM DIOXIDE; FERRIC OXIDE RED

HIGHLIGHTS OF PRESCRIBING INFORMATION

These highlights do not include all the information needed to use NEXAVAR safely and effectively. See full prescribing information for NEXAVAR.
NEXAVAR (sorafenib) tablets, for oral use
Initial U.S. Approval: 2005

1 INDICATIONS AND USAGE

NEXAVAR is a kinase inhibitor indicated for the treatment of

- Unresectable hepatocellular carcinoma (1.1)
- Advanced renal cell carcinoma (1.2)
- Locally recurrent or metastatic, progressive, differentiated thyroid carcinoma (DTC) refractory to radioactive iodine treatment (1.3)

2 DOSAGE AND ADMINISTRATION

The recommended dosage is 400 mg orally twice daily without food. (2.1)

3 DOSAGE FORMS AND STRENGTHS

Tablets: 200 mg (3)

4 CONTRAINDICATIONS

- NEXAVAR is contraindicated in patients with known severe hypersensitivity to sorafenib or any other component of NEXAVAR. (4)
- NEXAVAR in combination with carboplatin and paclitaxel is contraindicated in patients with squamous cell lung cancer. (4)

5 WARNINGS AND PRECAUTIONS

- Cardiovascular Events: Consider temporary or permanent discontinuation of NEXAVAR. (2.2, 5.1)
- Hemorrhage: Discontinue NEXAVAR if needed. (5.2)
- Hypertension: Monitor blood pressure weekly during the first 6 weeks and periodically thereafter. Consider temporary or permanent discontinuation for severe or persistent hypertension despite antihypertensive therapy. (5.3)
- Dermatologic Toxicities: Interrupt and/or decrease dose. Discontinue for severe or persistent reactions, or if Stevens-Johnson syndrome and toxic epidermal necrolysis is suspected. (5.4)
- Gastrointestinal Perforation: Discontinue NEXAVAR. (5.5)
- Risk of Impaired Wound Healing: Withhold NEXAVAR for at least 10 days prior to elective surgery. Do not administer for at least 2 weeks following major surgery and until adequate wound healing. The safety of resumption of NEXAVAR after resolution of wound healing complications has not been established. (5.7)
- QT Prolongation: Monitor electrocardiograms and electrolytes in patients at increased risk for ventricular arrhythmias. Correct electrolytes. Interrupt if QTc greater than 500 msec or increases greater than 60 msec from baseline. (2.2, 5.9, 12.2)
- Drug-Induced Liver Injury: Monitor liver function tests regularly; discontinue for unexplained transaminase elevations. (5.10)
- Embryo-Fetal Toxicity: NEXAVAR may cause fetal harm. Advise patients of the potential risk to a fetus and to use effective contraception. (5.11, 8.1, 8.3)
- Impairment of Thyroid Stimulating Hormone Suppression (TSH) in DTC: Monitor TSH monthly and adjust thyroid replacement therapy in patients with thyroid cancer. (5.12)

6 ADVERSE REACTIONS

The most common adverse reactions (≥20%) are diarrhea, fatigue, infection, alopecia, hand-foot skin reaction, rash, weight loss, decreased appetite, nausea, gastrointestinal and abdominal pains, hypertension, and hemorrhage. (6)

To report SUSPECTED ADVERSE REACTIONS, contact Bayer HealthCare Pharmaceuticals Inc. at 1-888-842-2937 or FDA at 1-800-FDA-1088 or www.fda.gov/medwatch.

7 DRUG INTERACTIONS

- Strong CYP3A Inducers: Avoid strong CYP3A4 inducers. (7.1)

8 USE IN SPECIFIC POPULATIONS

- Lactation: Advise women not to breastfeed. (8.2)

FULL PRESCRIBING INFORMATION

1 INDICATIONS AND USAGE

1.1 Hepatocellular Carcinoma

NEXAVAR® is indicated for the treatment of patients with unresectable hepatocellular carcinoma (HCC).

1.2 Renal Cell Carcinoma

NEXAVAR is indicated for the treatment of patients with advanced renal cell carcinoma (RCC).

1.3 Differentiated Thyroid Carcinoma

NEXAVAR is indicated for the treatment of patients with locally recurrent or metastatic, progressive, differentiated thyroid carcinoma (DTC) that is refractory to radioactive iodine treatment.

2 DOSAGE AND ADMINISTRATION

2.1 Recommended Dosage

The recommended dosage of NEXAVAR is 400 mg orally twice daily without food (at least 1 hour before or 2 hours after a meal) until the patient is no longer clinically benefiting from therapy or until unacceptable toxicity.

2.2 Dosage Modifications for Adverse Reactions

Recommended Dosage Modifications

The recommended dosage modifications for adverse reactions are provided in Tables 1, 2, and 3.

Table 1: Recommended Dose Reductions for Adverse Reactions
Dose Reduction | Hepatocellular Carcinoma and; Renal Cell Carcinoma | Differentiated Thyroid Carcinoma
First Dose Reduction | 400 mg orally once daily | 400 mg orally in the morning and 200 mg orally in the evening about 12 hours apart; OR; 200 mg orally in the morning and 400 mg orally in the evening about 12 hours apart
Second Dose Reduction | 200 mg orally once daily; OR; 400 every other day | 200 mg orally twice daily
Third Dose Reduction | None | 200 mg orally once daily

Table 2: Recommended Dosage Modifications of NEXAVAR for Adverse Reactions
Adverse Reaction | Severity^1 | NEXAVAR Dosage Modification
Cardiovascular Events [see Warnings and Precautions (5.1)]
Cardiac Ischemia and/or Infarction | Grade 2 and above | Permanently discontinue.
Congestive Heart Failure | Grade 3 | Interrupt^2 until Grade 1 or less, resume at reduced dose by 1 dose level.^3
Congestive Heart Failure | Grade 4 | Permanently discontinue.
Hemorrhage [see Warnings and Precautions (5.2)] | Grade 2 and above requiring medical intervention | Permanently discontinue.
Hypertension [see Warnings and Precautions (5.3)] | Grade 2 (symptomatic/persistent); OR; Grade 2 symptomatic increase by greater than 20 mm Hg (diastolic) or greater than 140/90 mm Hg if previously within normal limits; OR; Grade 3 | Interrupt until symptoms resolve and diastolic blood pressure less than 90 mm Hg, then resume at reduced dose by 1 dose level.^3; If needed, reduce another dose level.^3
Hypertension [see Warnings and Precautions (5.3)] | Grade 4 | Permanently discontinue.
Gastrointestinal Perforation [see Warnings and Precautions (5.5)] | Any grade | Permanently discontinue.
QT Interval Prolongation [see Warnings and Precautions (5.9)] | Greater than 500 milliseconds; OR; Increase from baseline of 60 milliseconds or greater | Interrupt and correct electrolyte abnormalities (magnesium, potassium, calcium).; Use medical judgement before restarting.
Drug-Induced Liver Injury [see Warnings and Precautions (5.10)] | Grade 3 ALT or higher in the absence of another cause^4; OR; AST/ALT greater than 3 × upper limit normal (ULN) with bilirubin greater than 2 × ULN in the absence of another cause^4 | Permanently discontinue.
Non-hematological toxicities [see Adverse Reactions (6.1)] | Grade 2 | Continue treatment at reduced dose by 1 dose level.
Non-hematological toxicities [see Adverse Reactions (6.1)] | Grade 3
Non-hematological toxicities [see Adverse Reactions (6.1)] | 1st occurrence | Interrupt until Grade 2 or less, then resume at reduced dose by 1 dose level.
Non-hematological toxicities [see Adverse Reactions (6.1)] | No improvement within 7 days; OR; 2nd or 3rd occurrence | Interrupt until Grade 2 or less, then resume at reduced dose by 2 dose levels.
Non-hematological toxicities [see Adverse Reactions (6.1)] | 4th occurrence | Interrupt until Grade 2 or less, then resume at reduced dose by 2 dose levels for HCC and RCC or 3 dose levels for DTC.
Non-hematological toxicities [see Adverse Reactions (6.1)] | Grade 4 | Permanently discontinue.

1 Adverse reactions graded according to National Cancer Institute Common Terminology Criteria for Adverse Events version 3.0 (NCI CTCAE v3.0).
2 If no recovery after 30 day interruption, discontinue treatment unless the patient is deriving clinical benefit.
3 If more than 2 dose reductions are required, permanently discontinue treatment.
4 In addition, any grade increased alkaline phosphatase in the absence of known bone pathology and Grade 2 or worse increased bilirubin; any 1 of the following: INR of 1.5 or greater, ascites and/or encephalopathy in the absence of underlying cirrhosis or other organ failure considered to be due to drug-induced liver injury.

Table 3: Recommended Dosage Modifications for Dermatologic Toxicities
Dermatologic Toxicity Grade | Occurrence | NEXAVAR Dosage Modification
Dermatologic Toxicity Grade |  | Hepatocellular and Renal Cell Carcinoma | Differentiated Thyroid Carcinoma
Grade 2: Painful erythema and swelling of the hands or feet and/or discomfort affecting the patient’s normal activities | 1st occurrence | Continue NEXAVAR and consider topical therapy for symptomatic relief.; If no improvement within 7 days, see below. | Decrease NEXAVAR to 600 mg daily. If no improvement within 7 days, see below.
Grade 2: Painful erythema and swelling of the hands or feet and/or discomfort affecting the patient’s normal activities | No improvement within 7 days at reduced dose; OR; 2nd and 3rd occurrence | Interrupt NEXAVAR until resolved or improved to Grade 0 to 1. | Interrupt NEXAVAR until completely resolved or improved to Grade1.
Grade 2: Painful erythema and swelling of the hands or feet and/or discomfort affecting the patient’s normal activities | No improvement within 7 days at reduced dose; OR; 2nd and 3rd occurrence | When resuming treatment, decrease dose by 1 dose level. | When resuming treatment, decrease dose by 1 dose level for 2nd occurrence and 2 doses levels for 3rd occurrence.
Grade 2: Painful erythema and swelling of the hands or feet and/or discomfort affecting the patient’s normal activities | 4th occurrence | Discontinue NEXAVAR treatment.
Grade 3: Moist desquamation, ulceration, blistering, or severe pain of the hands or feet, resulting in inability to work or perform activities of daily living | 1st occurrence | Interrupt NEXAVAR until resolved or improved to Grade 0 to 1 | Interrupt NEXAVAR until completely resolved or improved to Grade 1.
Grade 3: Moist desquamation, ulceration, blistering, or severe pain of the hands or feet, resulting in inability to work or perform activities of daily living | 1st occurrence | When resuming treatment, decrease dose by 1 dose level. | When resuming treatment, decrease dose by 1 dose level.
Grade 3: Moist desquamation, ulceration, blistering, or severe pain of the hands or feet, resulting in inability to work or perform activities of daily living | 2nd occurrence | Interrupt NEXAVAR until resolved or improved to Grade 0 to 1 | Interrupt NEXAVAR until completely resolved or improved to Grade 1.
Grade 3: Moist desquamation, ulceration, blistering, or severe pain of the hands or feet, resulting in inability to work or perform activities of daily living | 2nd occurrence | When resuming treatment, decrease dose by 1 dose level. | When resuming treatment, decrease dose by 2 dose levels.
 | 3rd occurrence | Discontinue NEXAVAR treatment.

Following improvement of Grade 2 or 3 dermatologic toxicity to Grade 0 or 1 for at least 28 days on a reduced dose of NEXAVAR, the dose of NEXAVAR may be increased 1 dose level from the reduced dose. Approximately 50% of patients requiring a dose reduction for dermatologic toxicity are expected to meet these criteria for resumption of the higher dose and roughly 50% of patients resuming the previous dose are expected to tolerate the higher dose (that is, maintain the higher dose level without recurrent Grade 2 or higher dermatologic toxicity).

3 DOSAGE FORMS AND STRENGTHS

Tablets:

- 200 mg sorafenib, round, biconvex, red film-coated tablets, debossed with the “Bayer cross” on one side and “200” on the other side.
- 200 mg sorafenib, round, faceted biconvex, red film-coated tablets, debossed with the “Bayer cross” on one side and “200” on the other side.

4 CONTRAINDICATIONS

- NEXAVAR is contraindicated in patients with known severe hypersensitivity to sorafenib or any other component of NEXAVAR.
- NEXAVAR in combination with carboplatin and paclitaxel is contraindicated in patients with squamous cell lung cancer [see Warnings and Precautions (5.8)].

5 WARNINGS AND PRECAUTIONS

5.1 Cardiovascular Events

In the SHARP (HCC) study, the incidence of cardiac ischemia/infarction was 2.7% in NEXAVAR-treated patients compared with 1.3% in those receiving placebo; in the TARGET (RCC) study, the incidence of cardiac ischemia/infarction was higher in the NEXAVAR-treated group (2.9%) compared with patients receiving placebo (0.4%), and in the DECISION (DTC) study, the incidence of cardiac ischemia/infarction was 1.9% in the NEXAVAR-treated group compared with 0% in patients receiving placebo. Patients with unstable coronary artery disease or recent myocardial infarction were excluded from this study. In multiple clinical trials, congestive heart failure has been reported in 1.9% of NEXAVAR-treated patients (N=2276) [see Adverse Reactions (6.2)].

Consider temporary or permanent discontinuation of NEXAVAR in patients who develop cardiovascular events [see Dosage and Administration (2.2)].

5.2 Hemorrhage

An increased risk of bleeding may occur following NEXAVAR administration. In the SHARP (HCC) study, the rates of bleeding from esophageal varices (2.4% and 4%) and of bleeding with a fatal outcome from any site (2.4% and 4%) were similar in NEXAVAR-treated patients and those receiving placebo, respectively . In the TARGET (RCC) study, bleeding was reported in 15.3% of patients in the NEXAVAR-treated group and 8.2% of patients receiving placebo. The incidence of Grade 3 and 4 bleeding was 2% and 0%, respectively, in NEXAVAR-treated patients, and 1.3% and 0.2%, respectively, in those receiving placebo. There was one fatal hemorrhage in each treatment group in the TARGET (RCC) study. In the DECISION (DTC) study, bleeding was reported in 17.4% of NEXAVAR-treated patients and 9.6% of those receiving placebo; however, the incidence of Grade 3 bleeding was similar (1% and 1.4%) in NEXAVAR-treated patients and in those receiving placebo.

If any bleeding necessitates medical intervention, consider permanent discontinuation of NEXAVAR [see Dosage and Administration (2.2)]. Due to the potential risk of bleeding, treat tracheal, bronchial, and esophageal infiltration with local therapy prior to administering NEXAVAR in patients with DTC.

5.3 Hypertension

In the SHARP (HCC) study, hypertension was reported in 9.4% of NEXAVAR-treated patients and 4.3% of patients receiving placebo. In the TARGET (RCC) study, hypertension was reported in 16.9% of NEXAVAR-treated patients and 1.8% of patients receiving placebo. In the DECISION (DTC) study, hypertension was reported in 40.6% of NEXAVAR-treated patients and 12.4% of patients receiving placebo. Hypertension was usually mild to moderate, occurred early in the course of treatment, and was managed with standard antihypertensive therapy. Permanent discontinuation due to hypertension occurred in 1 of 297 NEXAVAR-treated patients in the SHARP (HCC) study, 1 of 451 NEXAVAR-treated patients in the TARGET (RCC) study, and 1 of 207 NEXAVAR-treated patients in the DECISION (DTC) study.

Monitor blood pressure weekly during the first 6 weeks of NEXAVAR. Thereafter, monitor blood pressure and treat hypertension, if required, in accordance with standard medical practice. In cases of severe or persistent hypertension despite institution of antihypertensive therapy, consider temporary or permanent discontinuation of NEXAVAR [see Dosage and Administration (2.2)].

5.4 Dermatologic Toxicities

Hand-foot skin reaction and rash represent the most common adverse reactions attributed to NEXAVAR. Rash and hand-foot skin reaction are usually Grade 1 and 2 and generally appear during the first six weeks of treatment with NEXAVAR. Permanent discontinuation of therapy due to hand-foot skin reaction occurred in 4 (1.3%) of 297 NEXAVAR-treated patients with HCC, 3 (0.7%) of 451 NEXAVAR-treated patients with RCC, and 11 (5.3%) of 207 NEXAVAR-treated patients with DTC.

Management of dermatologic toxicities may include topical therapies for symptomatic relief, temporary treatment interruption and/or dose reduction of NEXAVAR, or in severe or persistent cases, permanent discontinuation of NEXAVAR [see Dosage and Administration (2.2)].

There have been reports of severe dermatologic toxicities, including Stevens-Johnson syndrome (SJS) and toxic epidermal necrolysis (TEN). These cases may be life-threatening. Discontinue NEXAVAR if SJS or TEN are suspected.

5.5 Gastrointestinal Perforation

Gastrointestinal perforation has been reported in less than 1% of patients taking NEXAVAR. In some cases this was not associated with apparent intra-abdominal tumor. In the event of a gastrointestinal perforation, permanently discontinue NEXAVAR.

5.6 Increased Risk of Bleeding with Concomitant Use of Warfarin

Infrequent bleeding or elevations in the International Normalized Ratio (INR) have been reported in some patients taking warfarin while on NEXAVAR. Monitor patients taking concomitant warfarin regularly for changes in prothrombin time (PT), INR or clinical bleeding episodes.

5.7 Risk of Impaired Wound Healing

Impaired wound healing can occur in patients who receive drugs that inhibit the VEGF signaling pathway. Therefore, NEXAVAR has the potential to adversely affect wound healing.

Withhold NEXAVAR for at least 10 days prior to elective surgery. Do not administer for at least 2 weeks following major surgery and until adequate wound healing. The safety of resumption of NEXAVAR after resolution of wound healing complications has not been established.

5.8 Increased Mortality Observed with NEXAVAR Administered in Combination with Carboplatin/Paclitaxel and Gemcitabine/Cisplatin in Squamous Cell Lung Cancer

In a subset analysis of two randomized controlled trials in chemo-naive patients with Stage IIIB-IV non-small cell lung cancer, patients with squamous cell carcinoma experienced higher mortality with the addition of NEXAVAR compared to those treated with carboplatin/paclitaxel alone (HR 1.81; 95% CI 1.19, 2.74) and gemcitabine/cisplatin alone (HR 1.22; 95% CI 0.82, 1.80). The use of NEXAVAR in combination with carboplatin/paclitaxel is contraindicated in patients with squamous cell lung cancer. NEXAVAR in combination with gemcitabine/cisplatin is not recommended in patients with squamous cell lung cancer. The safety and effectiveness of NEXAVAR has not been established in patients with non-small cell lung cancer.

5.9 QT Interval Prolongation

NEXAVAR can prolong the QT/QTc interval. QT/QTc interval prolongation increases the risk for ventricular arrhythmias.

Avoid NEXAVAR in patients with congenital long QT syndrome. Monitor electrolytes and electrocardiograms in patients with congestive heart failure, bradyarrhythmias, drugs known to prolong the QT interval, including Class Ia and III antiarrhythmics. Correct electrolyte abnormalities (magnesium, potassium, calcium). Interrupt NEXAVAR if QTc interval is greater than 500 milliseconds or for an increase from baseline of 60 milliseconds or greater [see Clinical Pharmacology (12.2)].

5.10 Drug-Induced Liver Injury

Sorafenib-induced hepatitis is characterized by a hepatocellular pattern of liver damage with significant increases of transaminases which may result in hepatic failure and death. Increases in bilirubin and INR may also occur. The incidence of severe drug-induced liver injury, defined as elevated transaminase levels above 20 times the upper limit of normal or transaminase elevations with significant clinical sequelae (for example, elevated INR, ascites, fatal, or transplantation), was two of 3,357 patients (0.06%) in a global monotherapy database.

Monitor liver function tests regularly. In case of significantly increased transaminases without alternative explanation, such as viral hepatitis or progressing underlying malignancy, discontinue NEXAVAR [see Dosage and Administration (2.2)].

5.11 Embryo-Fetal Toxicity

Based on its mechanism of action and findings in animals, NEXAVAR may cause fetal harm when administered to a pregnant woman. Sorafenib caused embryo-fetal toxicities in animals at maternal exposures that were significantly lower than the human exposures at the recommended dose of 400 mg twice daily. Advise pregnant women and females of reproductive potential of the potential risk to a fetus. Advise females of reproductive potential to use effective contraception during treatment and for 6 months following the last dose of NEXAVAR. Advise male patients with female partners of reproductive potential and pregnant partners to use effective contraception during treatment and for 3 months following the last dose of NEXAVAR [see Use in Specific Populations (8.1, 8.3)].

5.12 Impairment of Thyroid Stimulating Hormone Suppression in Differentiated Thyroid Carcinoma

NEXAVAR impairs exogenous thyroid suppression. In the DECISION (DTC) study, 99% of patients had a baseline thyroid stimulating hormone (TSH) level less than 0.5 mU/L. Elevation of TSH level above 0.5 mU/L was observed in 41% of NEXAVAR-treated patients as compared with 16% of those receiving placebo patients. For patients with impaired TSH suppression while receiving NEXAVAR, the median maximal TSH was 1.6 mU/L and 25% had TSH levels greater than 4.4 mU/L.

Monitor TSH levels monthly and adjust thyroid replacement medication as needed in patients with DTC.

6 ADVERSE REACTIONS

The following clinically significant adverse reactions are discussed elsewhere in the labeling:

- Cardiovascular events [see Warnings and Precautions (5.1)]
- Hemorrhage [see Warnings and Precautions (5.2)]
- Hypertension [see Warnings and Precautions (5.3)]
- Dermatologic toxicities [see Warnings and Precautions (5.4)]
- Gastrointestinal perforation [see Warnings and Precautions (5.5)]
- QT interval prolongation [see Warnings and Precautions (5.9) and Clinical Pharmacology (12.2)]
- Drug-induced liver injury [see Warnings and Precautions (5.10)]
- Impairment of TSH suppression in DTC [see Warnings and Precautions (5.12)]

6.1 Clinical Trials Experience

Because clinical trials are conducted under widely varying conditions, adverse reaction rates observed in the clinical trials of a drug cannot be directly compared to rates in the clinical trials of another drug and may not reflect the rates observed in practice.

The data described reflect exposure to NEXAVAR in 955 patients who participated in placebo-controlled studies in hepatocellular carcinoma (N=297), advanced renal cell carcinoma (N=451), or differentiated thyroid carcinoma (N = 207). The most common adverse reactions (≥20%), which were considered to be related to NEXAVAR, in patients with HCC, RCC or DTC are diarrhea, fatigue, infection, alopecia, hand-foot skin reaction, rash, weight loss, decreased appetite, nausea, gastrointestinal and abdominal pains, hypertension, and hemorrhage.

Hepatocellular Carcinoma

Table 4 shows the percentage of patients in the SHARP (HCC) study experiencing adverse reactions that were reported in at least 10% of patients and at a higher rate in the NEXAVAR-treated group than in those receiving placebo.

Table 4: Adverse Reactions Reported in at Least 10% of Patients and at a Higher Rate in NEXAVAR Arm than the Placebo Arm – SHARP (HCC)
Adverse Reaction^1 | NEXAVAR; N=297 |  |  | Placebo; N=302
Adverse Reaction^1 | All Grades % | Grade 3 % | Grade 4 % | All Grades % | Grade 3 % | Grade 4 %
Any Adverse Reaction | 98 | 39 | 6 | 96 | 24 | 8
Gastrointestinal
Diarrhea | 55 | 10 | <1 | 25 | 2 | 0
Anorexia | 29 | 3 | 0 | 18 | 3 | <1
Nausea | 24 | 1 | 0 | 20 | 3 | 0
Vomiting | 15 | 2 | 0 | 11 | 2 | 0
Constipation | 14 | 0 | 0 | 10 | 0 | 0
Constitutional symptoms
Fatigue | 46 | 9 | 1 | 45 | 12 | 2
Weight loss | 30 | 2 | 0 | 10 | 1 | 0
Pain
Pain, abdomen | 31 | 9 | 0 | 26 | 5 | 1
Dermatology/skin
Hand-foot skin reaction | 21 | 8 | 0 | 3 | <1 | 0
Rash/desquamation | 19 | 1 | 0 | 14 | 0 | 0
Alopecia | 14 | 0 | 0 | 2 | 0 | 0
Pruritus | 14 | <1 | 0 | 11 | <1 | 0
Dry skin | 10 | 0 | 0 | 6 | 0 | 0
Hepatobiliary/pancreas
Liver dysfunction | 11 | 2 | 1 | 8 | 2 | 1

1 Adverse reactions graded according to National Cancer Institute Common Terminology Criteria for Adverse Events version 3.0 (NCI CTCAE v3.0).

Hypertension was reported in 9% of patients treated with NEXAVAR and 4% of those receiving placebo. Grade 3 hypertension was reported in 4% of NEXAVAR-treated patients and 1% of those receiving placebo.

Hemorrhage/bleeding was reported in 18% of those receiving NEXAVAR and 20% of patients receiving placebo. The rates of Grade 3 and 4 bleeding were also higher in patients receiving placebo (Grade 3 – 3% NEXAVAR and 5% placebo and Grade 4 – 2% NEXAVAR and 4% placebo). Bleeding from esophageal varices was reported in 2.4% in NEXAVAR-treated patients and 4% of patients receiving placebo.

Renal failure was reported in <1% of patients treated with NEXAVAR and 3% of patients receiving placebo. Clinical pancreatitis was reported in 1 of 297 NEXAVAR-treated patients (Grade 2).

The rate of adverse reactions (including those associated with progressive disease) resulting in permanent discontinuation was similar in both the NEXAVAR-treated patients and those receiving placebo (32% of NEXAVAR-treated patients and 35% of patients receiving placebo).

Laboratory test abnormalities reported in SHARP are presented in Table 5.

Table 5: Laboratory Test Abnormalities Reported in SHARP (HCC)
Laboratory Parameter^1 | NEXAVAR; N=297 |  | Placebo; N=302
Laboratory Parameter^1 | All Grades; (%) | Grade 3 or 4 (%) | All Grades; (%) | Grade 3 or 4 (%)
Hypoalbuminemia | 59 | 0 | 47 | 0
Elevated Lipase | 40 | 9 | 37 | 9
Lymphopenia | 47 | NR | 42 | NR
Thrombocytopenia | 46 | 4 | 41 | <1
Elevated INR | 42 | 4 | 34 | 2
Hypophosphatemia | 35 | 11 | 11 | 2
Elevated Amylase | 34 | 2 | 29 | 2
Hypocalcemia | 27 | 2.4 | 15 | 1
Hypokalemia | 10 | <1 | 6 | <1

1- Laboratory parameters graded according to National Cancer Institute Common Terminology Criteria for Adverse Events version 3.0 (NCI CTCAE v3.0).

NR = not reported

Renal Cell Carcinoma

Table 6 shows the percentage of patients in the TARGET (RCC) study experiencing adverse reactions that were reported in at least 10% of patients and at a higher rate in NEXAVAR-treated patients arm than in those receiving placebo.

The rate of adverse reactions (including those associated with progressive disease) resulting in permanent discontinuation was similar in both the NEXAVAR-treated patients and patients receiving placebo (10% and 8%, respectively).

Clinical pancreatitis was reported in 3 of 451 NEXAVAR-treated patients (one Grade 2 and two Grade 4).

Table 6: Adverse Reactions Reported in at Least 10% of Patients and at a Higher Rate in NEXAVAR Arm than the Placebo Arm – TARGET (RCC)
Adverse Reaction^1 | NEXAVAR; N=451 |  |  | Placebo; N=451
Adverse Reaction^1 | All Grades; % | Grade 3; % | Grade 4; % | All Grades; % | Grade 3; % | Grade 4; %
Any Adverse Reactions | 95 | 31 | 7 | 86 | 22 | 6
Gastrointestinal symptoms
Diarrhea | 43 | 2 | 0 | 13 | <1 | 0
Nausea | 23 | <1 | 0 | 19 | <1 | 0
Anorexia | 16 | <1 | 0 | 13 | 1 | 0
Vomiting | 16 | <1 | 0 | 12 | 1 | 0
Constipation | 15 | <1 | 0 | 11 | <1 | 0
Dermatology/skin
Rash/desquamation | 40 | <1 | 0 | 16 | <1 | 0
Hand-foot skin reaction | 30 | 6 | 0 | 7 | 0 | 0
Alopecia | 27 | <1 | 0 | 3 | 0 | 0
Pruritus | 19 | <1 | 0 | 6 | 0 | 0
Dry skin | 11 | 0 | 0 | 4 | 0 | 0
Constitutional symptoms
Fatigue | 37 | 5 | <1 | 28 | 3 | <1
Weight loss | 10 | <1 | 0 | 6 | 0 | 0
Cardiovascular, General
Hypertension | 17 | 3 | <1 | 2 | <1 | 0
Hemorrhage/bleeding
Hemorrhage – all sites | 15 | 2 | 0 | 8 | 1 | <1
Pulmonary
Dyspnea | 14 | 3 | <1 | 12 | 2 | <1
Neurology
Neuropathy-sensory | 13 | <1 | 0 | 6 | <1 | 0
Pain
Pain, abdomen | 11 | 2 | 0 | 9 | 2 | 0
Pain, headache | 10 | <1 | 0 | 6 | <1 | 0
Pain, joint | 10 | 2 | 0 | 6 | <1 | 0

1 Adverse reactions graded according to National Cancer Institute Common Terminology Criteria for Adverse Events version 3.0 (NCI CTCAE v3.0).

Laboratory test abnormalities reported in TARGET are presented in Table 7.

Table 7: Laboratory Test Abnormalities Reported in TARGET (RCC)
Laboratory Parameter^1 | NEXAVAR; N=451 |  | Placebo; N=451
Laboratory Parameter^1 | All Grades; (%) | Grade 3 or 4 (%) | All Grades; (%) | Grade 3 or 4 (%)
Hypophosphatemia | 45 | 13 | 11 | 3
Anemia | 44 | 2 | 49 | 4
Elevated Lipase | 41 | 12 | 30 | 7
Elevated Amylase | 30 | 1 | 23 | 3
Lymphopenia | 23 | 13 | 13 | 7
Neutropenia | 18 | 5 | 10 | 2
Thrombocytopenia | 12 | 1 | 5 | 0
Hypocalcemia | 12 | 2 | 8 | <1
Hypokalemia | 5 | 1 | <1 | <1

1 Laboratory parameters graded according to National Cancer Institute Common Terminology Criteria for Adverse Events version 3.0 (NCI CTCAE v3.0).

Differentiated Thyroid Carcinoma

The safety of NEXAVAR was evaluated in DECISION in 416 patients with locally recurrent or metastatic, progressive differentiated thyroid carcinoma (DTC) refractory to radioactive iodine (RAI) treatment randomized to receive 400 mg twice daily NEXAVAR (n=207) or matching placebo (n=209) until disease progression or intolerable toxicity in a double-blind trial [see Clinical Studies (14.3)]. The data described below reflect a median exposure to NEXAVAR for 46 weeks (range 0.3 to 135). The population exposed to NEXAVAR was 50% male, and had a median age of 63 years.

Dose interruptions for adverse reactions were required in 66% of patients receiving NEXAVAR and dose reductions were required in 64% of patients. Adverse reactions that resulted in treatment discontinuation were reported in 14% of NEXAVAR-treated patients compared to 1.4% of patients receiving placebo.

Table 8 shows the percentage of DTC patients experiencing adverse reactions at a higher rate in NEXAVAR-treated patients than in patients receiving placebo in the double-blind phase of the DECISION study. Grade 3 adverse reactions occurred in 53% of NEXAVAR-treated patients compared to 23% of patients receiving placebo. Grade 4 adverse reactions occurred in 12% of NEXAVAR-treated patients compared to 7% of patients receiving placebo.

Table 8: Selected Adverse Reactions Occurring at a Higher Incidence in NEXAVAR-Treated Patients [Between Arm Difference of ≥ 5% (All Grades)1 or ≥ 2% (Grades 3 and 4)]
Adverse Reaction |  | NEXAVAR N = 207 |  | Placebo N = 209
Adverse Reaction |  | All Grades (%) | Grades 3 and 4 (%) | All Grades (%) | Grades 3 and 4 (%)
Skin and subcutaneous tissue disorders
 | PPES^5 | 69 | 19 | 8 | 0
 | Alopecia | 67 | 0 | 8 | 0
 | Rash | 35 | 5 | 7 | 0
 | Pruritus | 20 | 0.5 | 11 | 0
 | Dry skin | 13 | 0.5 | 5 | 0
 | Erythema | 10 | 0 | 0.5 | 0
 | Hyperkeratosis | 7 | 0 | 0 | 0
Gastrointestinal disorders
 | Diarrhea | 68 | 6 | 15 | 1
 | Stomatitis^3 | 24 | 2 | 3 | 0
 | Nausea | 21 | 0 | 12 | 0
 | Abdominal pain^2 | 20 | 1 | 7 | 1
 | Constipation | 16 | 0 | 8 | 0.5
 | Oral pain^4 | 14 | 0.5 | 6 | 0
 | Vomiting | 11 | 0 | 3 | 0
Investigations
 | Weight loss | 49 | 6 | 14 | 1
General disorders and administration site conditions
 | Fatigue | 41 | 5 | 20 | 1
 | Asthenia | 12 | 0 | 7 | 0
 | Pyrexia | 11 | 1 | 5 | 0
Vascular disorders
 | Hypertension^6 | 41 | 10 | 12 | 2
Metabolism and nutrition disorders
 | Decreased appetite | 30 | 2 | 5 | 0
Nervous system disorders
 | Headache | 17 | 0 | 6 | 0
 | Dysgeusia | 6 | 0 | 0 | 0
Musculoskeletal and connective tissue disorders
 | Pain in extremity | 15 | 1 | 7 | 0
 | Muscle spasms | 10 | 0 | 3 | 0
Respiratory, thoracic and mediastinal disorders
 | Dysphonia | 13 | 0.5 | 3 | 0
 | Epistaxis | 7 | 0 | 1 | 0
Neoplasms benign, malignant and unspecified
 | Squamous cell carcinoma of skin | 3 | 3 | 0 | 0

1 National Cancer Institute Common Terminology Criteria for Adverse Events Version 3.0
2 Includes the following terms: abdominal pain, abdominal discomfort, hepatic pain, esophageal pain, esophageal discomfort, abdominal pain lower, abdominal pain upper, abdominal tenderness, abdominal rigidity
3 Includes the following terms: stomatitis, aphthous stomatitis, mouth ulceration, mucosal inflammation
4 Includes the following terms: oral pain, oropharyngeal discomfort, glossitis, burning mouth syndrome, glossodynia
5 Palmar-plantar erythrodysesthesia syndrome (Hand-foot skin reaction)
6 Includes the following terms: hypertension, blood pressure increased, blood pressure systolic increased

The relative increase for the following laboratory abnormalities observed in NEXAVAR-treated patients as compared to patients receiving placebo in the DECISION study is similar to that observed in the RCC and HCC studies: lipase, amylase, hypokalemia, hypophosphatemia, neutropenia, lymphopenia, anemia, and thrombocytopenia. Hypocalcemia was more frequent and more severe in patients with DTC, especially those with a history of hypoparathyroidism, compared to patients with RCC or HCC. Other laboratory test abnormalities reported in DECISION are presented in Table 9

Table 9: Laboratory Test Abnormalities Reported in DECISION (DTC
Laboratory Parameter^1 | NEXAVAR; N=207 |  | Placebo; N=209
Laboratory Parameter^1 | All Grades; (%) | Grade 3 or 4 (%) | All Grades; (%) | Grade 3 or 4 (%)
Elevated ALT | 59 | 4 | 24 | 0
Elevated AST | 54 | 2 | 15 | 0
Hypocalcemia | 36 | 10 | 11 | 3

1 Laboratory parameters graded according to National Cancer Institute Common Terminology Criteria for Adverse Events version 3.0 (NCI CTCAE v3.0).

Additional Data from Multiple Clinical Trials

The following additional drug-related adverse reactions and laboratory abnormalities were reported from clinical trials of NEXAVAR (very common 10% or greater, common 1 to less than 10%, uncommon 0.1% to less than 1%, rare less than 0.1 %):

Cardiovascular: Common: congestive heart failure*†, myocardial ischemia and/or infarction Uncommon: hypertensive crisis* Rare: QT prolongation*

Dermatologic: Very common: erythema Common: exfoliative dermatitis, acne, flushing, folliculitis, hyperkeratosis Uncommon: eczema, erythema multiforme

Digestive: Very common: increased lipase, increased amylase Common: mucositis, stomatitis (including dry mouth and glossodynia), dyspepsia, dysphagia, gastrointestinal reflux Uncommon: pancreatitis, gastritis, gastrointestinal perforations*, cholecystitis, cholangitis

Note that elevations in lipase are very common (41%, see below); a diagnosis of pancreatitis should not be made solely on the basis of abnormal laboratory values

General Disorders: Very common: infection, hemorrhage (including gastrointestinal* and respiratory tract* and uncommon cases of cerebral hemorrhage*), asthenia, pain (including mouth, bone, and tumor pain), pyrexia, decreased appetite Common: influenza-like illness

Hematologic: Very common: leukopenia, lymphopenia Common: anemia, neutropenia, thrombocytopenia Uncommon: INR abnormal

Hepatobiliary disorders: Rare: drug-induced liver injury (including hepatic failure and death)

Hypersensitivity: Uncommon: hypersensitivity reactions (including skin reactions and urticaria), anaphylactic reaction

Metabolic and Nutritional: Very common: hypophosphatemia Common: transient increases in transaminases, hypocalcemia, hypokalemia, hyponatremia, hypothyroidism Uncommon: dehydration, transient increases in alkaline phosphatase, increased bilirubin (including jaundice), hyperthyroidism

Musculoskeletal: Very common: arthralgia Common: myalgia, muscle spasms

Nervous System and Psychiatric: Common: depression, dysgeusia Uncommon: tinnitus, reversible posterior leukoencephalopathy*

Renal and Genitourinary: Common: renal failure, proteinuria Rare: nephrotic syndrome

Reproductive: Common: erectile dysfunction Uncommon: gynecomastia

Respiratory: Common: rhinorrhea Uncommon: interstitial lung disease-like events (includes reports of pneumonitis, radiation pneumonitis, acute respiratory distress, interstitial pneumonia, pulmonitis and lung inflammation)

In addition, the following medically significant adverse reactions were uncommon during clinical trials of NEXAVAR: transient ischemic attack, arrhythmia, and thromboembolism. For these adverse reactions, the causal relationship to NEXAVAR has not been established.

*adverse reactions may have a life-threatening or fatal outcome.

†reported in 1.9% of patients treated with NEXAVAR (N= 2276).

6.2 Postmarketing Experience

The following adverse reactions have been identified during postapproval use of NEXAVAR. Because these reactions are reported voluntarily from a population of uncertain size, it is not always possible to reliably estimate their frequency or establish a causal relationship to drug exposure.

Blood and lymphatic disorders: Thrombotic microangiopathy (TMA)

Dermatologic: Stevens-Johnson syndrome and toxic epidermal necrolysis (TEN)

Hypersensitivity: Angioedema

Musculoskeletal: Rhabdomyolysis, osteonecrosis of the jaw

Respiratory: Interstitial lung disease-like events (which may have a life-threatening or fatal outcome)

Vascular: Arterial (including aortic) aneurysms, dissections, and rupture

7 DRUG INTERACTIONS

7.1 Effect of Other Drugs on NEXAVAR

Strong CYP3A4 Inducers

The concomitant use of NEXAVAR with rifampin, a strong CYP3A4 inducer decreased the mean AUC of sorafenib, which may decrease the antitumor activity [see Clinical Pharmacology (12.3)]. Avoid concomitant use of NEXAVAR with strong CYP3A4 inducers, when possible, because these drugs can decrease the systemic exposure to sorafenib.

Neomycin

The concomitant use of NEXAVAR with neomycin decreased the mean AUC of sorafenib, which may decrease the antitumor activity. Avoid concomitant use of NEXAVAR with neomycin. The effects of other antibiotics on the pharmacokinetics of sorafenib have not been studied [see Clinical Pharmacology (12.3)].

7.2 Concomitant Use of Warfarin

The concomitant use of NEXAVAR and warfarin may increase the risk of bleeding or increased the INR. Monitor INR and for clinical bleeding episodes in patients taking warfarin while receiving NEXAVAR [see Warnings and Precautions (5.6)].

7.3 Drugs That Prolong the QT Interval

NEXAVAR is associated with QTc interval prolongation. Avoid coadministration of NEXAVAR with medicinal products with a known potential to prolong QT/QTc interval [see Warnings and Precautions (5.9), Clinical Pharmacology (12.2)].

8 USE IN SPECIFIC POPULATIONS

8.1 Pregnancy

Risk Summary

Based on findings from animal studies and its mechanism of action[see Clinical Pharmacology (12.1)], NEXAVAR may cause fetal harm when administered to a pregnant woman. There are no available data in pregnant women to inform a drug-associated risk. In animal reproduction studies, oral administration of sorafenib to pregnant rats and rabbits during the period of organogenesis resulted in embryo-fetal toxicities at maternal exposures that were significantly lower than human exposures at the recommended dose of 400 mg twice daily (see Data). Advise pregnant women and females of reproductive potential of the potential risk to a fetus.

The background risk of major birth defects and miscarriage for the indicated population is unknown. In the U.S. general population, the estimated background risk of major birth defects and miscarriage in clinically recognized pregnancies is 2% to 4% and 15% to 20%, respectively.

Data

Animal Data

In animal reproduction studies, sorafenib was teratogenic and induced embryo-fetal toxicity (including increased post-implantation loss, resorptions, skeletal retardations, and retarded fetal weight) when administered orally to pregnant rats and rabbits during the period of organogenesis. The effects occurred at doses considerably below the recommended human dose of 400 mg twice daily (approximately 500 mg/m^2/day on a body surface area basis). Adverse intrauterine development effects were seen at doses >0.2 .mg/kg/day (1.2 mg/m^2/day) in rats and ≥0.3 mg/kg/day (≥3.6 mg/m^2/day) in rabbits. These doses result in exposures (AUC) that are approximately 0.008 times the AUC in patients at the recommended dose.

8.2 Lactation

Data

Animal Data

Following administration of radiolabeled sorafenib to lactating Wistar rats, approximately 27% of the radioactivity was secreted into milk. The milk to plasma AUC ratio was approximately 5:1.

8.3 Females and Males of Reproductive Potential

Pregnancy Testing

Verify the pregnancy status of females of reproductive potential prior to the initiation of NEXAVAR.

Contraception

Females

Advise females of reproductive potential to use effective contraception during treatment and for 6 months following the last dose of NEXAVAR.

Males

Based on genotoxicity and findings in animal reproduction studies, advise males with female partners of reproductive potential and pregnant partners to use effective contraception during treatment with NEXAVAR and for 3 months following the last dose of NEXAVAR [see Use in Specific Populations (8.1), Nonclinical Toxicology (13.1)].

Infertility

Males

Based on findings in animal studies, NEXAVAR may impair fertility in males of reproductive potential [see Nonclinical Toxicology (13.1)].

8.4 Pediatric Use

The safety and effectiveness of NEXAVAR have not been established in pediatric patients.

Juvenile Animal Toxicity Data

Repeat dosing of sorafenib to young and growing dogs resulted in irregular thickening of the femoral growth plate at daily sorafenib doses ≥600 mg/m^2 (approximately 0.3 times the AUC at the recommended human dose), hypocellularity of the bone marrow adjoining the growth plate at 200 mg/m^2/day (approximately 0.1 times the AUC at the recommended human dose), and alterations of the dentin composition at 600 mg/m^2/day. Similar effects were not observed in adult dogs when dosed for 4 weeks or less.

8.5 Geriatric Use

In total, 59% of HCC patients treated with NEXAVAR were age 65 years or older and 19% were 75 and older. In total, 32% of RCC patients treated with NEXAVAR were age 65 years or older and 4% were 75 and older. No differences in safety or efficacy were observed between older and younger patients, and other reported clinical experience has not identified differences in responses between the elderly and younger patients, but greater sensitivity of some older individuals cannot be ruled out.

8.6 Renal Impairment

No dose adjustment is necessary for patients with mild, moderate or severe renal impairment who are not on dialysis.The pharmacokinetics of sorafenib have not been studied in patients who are on dialysis [see Clinical Pharmacology (12.3)].

8.7 Hepatic Impairment

No dose adjustment is necessary for patients with mild or moderate hepatic impairment. The pharmacokinetics of sorafenib have not been studied in patients with severe (Child-Pugh C) hepatic impairment [see Clinical Pharmacology (12.3)].

10 OVERDOSAGE

The adverse reactions observed at a dose of 800 mg twice daily (2 times the recommended dose) were primarily diarrhea and dermatologic. No information is available on symptoms of acute overdose in animals because of the saturation of absorption in oral acute toxicity studies conducted in animals.

In cases of suspected overdose, withhold NEXAVAR and institute supportive care.

11 DESCRIPTION

Sorafenib, a kinase inhibitor, is the tosylate salt of sorafenib. Sorafenib tosylate has the chemical name 4-(4-{3-[4-Chloro-3-(trifluoromethyl)phenyl]ureido}phenoxy)N2-methylpyridine-2-carboxamide 4-methylbenzenesulfonate. The molecular formula of sorafenib tosylate is C21H16ClF3N4O3 x C7H8O3S and the molecular weight of sorafenib tosylate is 637.0 g/mole. Its structural formula is:

Sorafenib tosylate is a white to yellowish or brownish solid. Sorafenib tosylate is practically insoluble in aqueous media, slightly soluble in ethanol and soluble in PEG 400.

NEXAVAR (sorafenib), for oral use is supplied as film-coated tablets containing 200 mg sorafenib equivalent to 274 mg sorafenib tosylate and the following inactive ingredients: croscarmellose sodium, ferric oxide red, hypromellose, magnesium stearate, microcrystalline cellulose, polyethylene glycol sodium lauryl sulphate, and titanium dioxide.

12 CLINICAL PHARMACOLOGY

12.1 Mechanism of Action

Sorafenib is a kinase inhibitor that decreases tumor cell proliferation in vitro. Sorafenib was shown to inhibit multiple intracellular (c-CRAF, BRAF and mutant BRAF) and cell surface kinases (KIT, FLT- 3, RET, RET/PTC, VEGFR-1, VEGFR- 2, VEGFR- 3, and PDGFR-ß). Several of these kinases are thought to be involved in tumor cell signaling, angiogenesis and apoptosis. Sorafenib inhibited tumor growth of HCC, RCC, and DTC human tumor xenografts in immunocompromised mice. Reductions in tumor angiogenesis were seen in models of HCC and RCC upon sorafenib treatment, and increases in tumor apoptosis were observed in models of HCC, RCC, and DTC.

12.2 Pharmacodynamics

Cardiac Electrophysiology

The effect of NEXAVAR 400 mg twice daily on the QTc interval was evaluated in a multi-center, open-label, non-randomized trial in 53 patients with advanced cancer. No large changes in the mean QTc intervals (that is, >20 ms) from baseline were detected in the trial. After one 28-day treatment cycle, the largest mean QTc interval change of 8.5 ms (upper bound of two-sided 90% confidence interval, 13.3 ms) was observed at 6 hours post-dose on day 1 of cycle 2 [see Warnings and Precautions (5.9), Drug Interactions (7.3)].

12.3 Pharmacokinetics

Multiple doses of NEXAVAR for 7 days resulted in a 2.5- to 7-fold accumulation compared to a single dose. Steady-state plasma sorafenib concentrations were achieved within 7 days, with a peak-to-trough ratio of mean concentrations of less than 2.

The steady-state concentrations of sorafenib following administration of NEXAVAR 400 mg twice daily were evaluated in DTC, RCC and HCC patients. Patients with DTC have mean steady-state concentrations that are 1.8-fold higher than patients with HCC and 2.3-fold higher than those with RCC. The reason for increased sorafenib concentrations in DTC patients is unknown.

Mean Cmax and AUC increased less than proportionally beyond oral doses of 400 mg administered twice daily.

Absorption

After administration of NEXAVAR tablets, the mean relative bioavailability was 38–49% when compared to an oral solution. Following oral administration, sorafenib reached peak plasma levels in approximately 3 hours.

Effects of Food

With a moderate-fat meal (30% fat; 700 calories), bioavailability was similar to that in the fasted state. With a high-fat meal (50% fat; 900 calories), bioavailability was reduced by 29% compared to that in the fasted state.

Distribution

In vitro binding of sorafenib to human plasma proteins was 99.5%.

Elimination

The mean elimination half-life of sorafenib was approximately 25 to 48 hours.

Metabolism

Sorafenib undergoes oxidative metabolism by hepatic CYP3A4, as well as glucuronidation by UGT1A9.

Excretion

Sorafenib accounted for approximately 70–85% of the circulating analytes in plasma at steady-state. Eight metabolites of sorafenib have been identified, of which 5 have been detected in plasma. The main circulating metabolite of sorafenib, the pyridine N-oxide that comprises approximately 9–16% of circulating analytes at steady-state, showed in vitro potency similar to that of sorafenib.

Following oral administration of a 100 mg dose of a solution formulation of sorafenib, 96% of the dose was recovered within 14 days, with 77% of the dose excreted in feces and 19% of the dose excreted in urine as glucuronidated metabolites. Unchanged sorafenib, accounting for 51% of the dose, was found in feces but not in urine.

Specific Populations

A study of the pharmacokinetics of sorafenib indicated that the mean AUC of sorafenib in Asians (N=78) was 30% lower than in Whites (N=40). Sex and age do not have a clinically meaningful effect on the pharmacokinetics of sorafenib.

Patients with Renal Impairment

Mild (CLcr 50-80 mL/min), moderate (CLcr 30 - <50 mL/min), and severe (CLcr <30 mL/min) renal impairment do not affect the pharmacokinetics of sorafenib [see Use in Specific Populations (8.6)].

Patients with Hepatic Impairment

Mild (Child-Pugh A) and moderate (Child-Pugh B) hepatic impairment do not affect the pharmacokinetics of sorafenib [see Use in Specific Populations (8.7)].

Drug Interactions Studies

Effect of Strong CYP3A4 Inhibitors on Sorafenib: Ketoconazole, a strong inhibitor of CYP3A4 and P-glycoprotein, administered at a dose of 400 not alter the mean AUC of a single oral dose of NEXAVAR 50 mg in healthy subjects.

Effect of Strong CYP3A4 Inducers on Sorafenib: Concomitant use of NEXAVAR with rifampin administered at a dose of 600 mg once daily for 5 days with a single oral dose of NEXAVAR 400 mg in healthy volunteers resulted in a 37% decrease in the mean AUC of sorafenib.

Effect of Neomycin on Sorafenib: Neomycin administered as an oral dose of 1 g three times daily for 5 days decreased the mean AUC of sorafenib by 54% in healthy subjects administered a single oral dose of NEXAVAR 400 mg.

Effect of Sorafenib on Other Drugs: NEXAVAR 400 mg twice daily for 28 days did not increase the systemic exposure of concomitantly administered midazolam (CYP3A4 substrate), dextromethorphan (CYP2D6 substrate), and omeprazole (CYP2C19 substrate) [see Clinical Pharmacology (12.3)].

Drugs that Increase Gastric pH: The aqueous solubility of sorafenib is pH dependent, with higher pH resulting in lower solubility. However, omeprazole, a proton pump inhibitor, administered at a dose of 40 mg once daily for 5 days, did not result in a clinically meaningful change in sorafenib single dose exposure.

In Vitro Studies

Sorafenib competitively inhibited CYP2B6, CYP2C8, CYP2C9, CYP2C19, CYP2D6, and CYP3A4 in vitro. However, NEXAVAR 400 mg twice daily for 28 days with substrates of CYP3A4, CYP2D6 and CYP2C19 did not increase the systemic exposure of these substrates [see Drug Interactions (7.3)].

Sorafenib did not increase CYP1A2 and CYP3A4 activities, suggesting that sorafenib is unlikely to induce CYP1A2 or CYP3A4 in humans.

Sorafenib inhibits glucuronidation by UGT1A1 and UGT1A9 in vitro. NEXAVAR could increase the systemic exposure of concomitantly administered drugs that are UGT1A1 or UGT1A9 substrates.

Sorafenib inhibited P-glycoprotein in vitro. NEXAVAR could increase the concentrations of concomitantly administered drugs that are P-glycoprotein substrates.

13 NONCLINICAL TOXICOLOGY

13.1 Carcinogenesis, Mutagenesis, Impairment of Fertility

Carcinogenicity studies have not been performed with sorafenib. Sorafenib was clastogenic when tested in an in vitro mammalian cell assay (Chinese hamster ovary) in the presence of metabolic activation. Sorafenib was not mutagenic in the in vitro Ames bacterial cell assay or clastogenic in an in vivo mouse micronucleus assay. One intermediate in the manufacturing process, which is also present in the final drug substance (<0.15%), was positive for mutagenesis in an in vitro bacterial cell assay (Ames test) when tested independently.

No specific studies with sorafenib have been conducted in animals to evaluate the effect on fertility. However, results from the repeat-dose toxicity studies suggest there is a potential for sorafenib to impair reproductive function and fertility. Multiple adverse effects were observed in male and female reproductive organs, with the rat being more susceptible than mice or dogs. Typical changes in rats consisted of testicular atrophy or degeneration, degeneration of epididymis, prostate, and seminal vesicles, central necrosis of the corpora lutea and arrested follicular development. Sorafenib-related effects on the reproductive organs of rats were manifested at daily oral doses ≥ 5 mg/kg (30 mg/m^2). This dose results in an exposure (AUC) that is approximately 0.5 times the AUC in patients at the recommended human dose. Dogs showed tubular degeneration in the testes at 30 mg/kg/day (600 mg/m^2/day). This dose results in an exposure that is approximately 0.3 times the AUC at the recommended human dose. Oligospermia was observed in dogs at 60 mg/kg/day (1200 mg/m^2/day) of sorafenib.

14 CLINICAL STUDIES

14.1 Hepatocellular Carcinoma

The SHARP (HCC) study (NCT00105443) was an international, multicenter, randomized, double blind, placebo-controlled trial in patients with unresectable hepatocellular carcinoma. Overall survival was the primary endpoint. A total of 602 patients were randomized; 299 to NEXAVAR 400 mg twice daily and 303 to matching placebo. All 602 randomized subjects were included in the ITT population for the efficacy analyses.

Demographics and baseline disease characteristics were similar between the NEXAVAR and placebo arms with regard to age, gender, race, performance status, etiology (including hepatitis B, hepatitis C and alcoholic liver disease), TNM stage (stage I: <1% vs. <1%; stage II: 10.4% vs. 8.3%; stage III: 37.8% vs. 43.6%; stage IV: 50.8% vs. 46.9%), absence of both macroscopic vascular invasion and extrahepatic tumor spread (30.1% vs. 30.0%), and Barcelona Clinic Liver Cancer stage (stage B: 18.1% vs. 16.8%; stage C: 81.6% vs. 83.2%; stage D: <1% vs. 0%). Liver impairment by Child-Pugh score was comparable between the NEXAVAR and placebo arms (Class A: 95% vs. 98%; B: 5% vs. 2%). Only one patient with Child-Pugh class C was entered. Prior treatments included surgical resection procedures (19.1% vs. 20.5%), locoregional therapies (including radiofrequency ablation, percutaneous ethanol injection and transarterial chemoembolization; 38.8% vs. 40.6%), radiotherapy (4.3% vs. 5.0%) and systemic therapy (3.0% vs. 5.0%).

The trial was stopped for efficacy following a pre-specified second interim analysis for survival showing a statistically significant advantage for NEXAVAR over placebo for overall survival (HR: 0.69, p= 0.00058) (see Table 10 and Figure 1). This advantage was consistent across all subsets analyzed.

Final analysis of time to tumor progression (TTP) based on data from an earlier time point (by independent radiologic review) also was significantly longer in the NEXAVAR arm (HR: 0.58, p=0.000007) (see Table 10).

Table 10: Efficacy Results from SHARP (HCC)
Efficacy Parameter | NEXAVAR; (N=299) | Placebo; (N=303)
Overall Survival
Number of Events | 143 | 178
Median, months | 10.7 | 7.9
(95% CI) | (9.4, 13.3) | (6.8, 9.1)
Hazard Ratio^1 (95% CI) | 0.69 (0.55, 0.87)
P-value (log-rank test^2) | 0.00058
Time to Progression ^3
Number of Events | 107 | 156
Median, months | 5.5 | 2.8
(95% CI) | (4.1, 6.9) | (2.7, 3.9)
Hazard Ratio^1 (95% CI) | 0.58; (0.45, 0.74)
P-value (log-rank test^2) | 0.000007

CI=Confidence interval

1 Hazard ratio, sorafenib/placebo, stratified Cox model
2 Stratified log rank (for the interim analysis of survival, the stopping boundary one-sided alpha = 0.0077)
3 The time-to-progression (TTP) analysis, based on independent radiologic review, was based on data from an earlier time point than the survival analysis

Figure 1: Kaplan-Meier Curve of Overall Survival in SHARP (HCC) (Intent-to-Treat Population)

14.2 Renal Cell Carcinoma

The safety and efficacy of NEXAVAR in the treatment of advanced renal cell carcinoma (RCC) were studied in the following two randomized controlled clinical trials.

TARGET

TARGET (NCT00073307) was an international, multicenter, randomized, double blind, placebo-controlled trial in patients with advanced renal cell carcinoma who had received one prior systemic therapy. Primary study endpoints included overall survival and progression-free survival (PFS). Tumor response rate was a secondary endpoint. The PFS analysis included 769 patients, per protocol, stratified by MSKCC (Memorial Sloan Kettering Cancer Center) prognostic risk category (low or intermediate) and country and randomized to NEXAVAR 400 mg twice daily (N=384) or to placebo (N=385).

Table 11 summarizes the demographic and disease characteristics of the study population analyzed. Baseline demographics and disease characteristics were well balanced for both treatment groups. The median time from initial diagnosis of RCC to randomization was 1.6 and 1.9 years for the NEXAVAR and placebo arms, respectively.

Table 11: Demographic and Disease Characteristics – TARGET (RCC)
Characteristics | NEXAVAR; N=384 |  | Placebo; N=385
 | N | (%) | N | (%)
Gender
Male | 267 | (70) | 287 | (75)
Female | 116 | (30) | 98 | (25)
Race
White | 276 | (72) | 278 | (73)
Black/Asian/ Hispanic/Other | 11 | (3) | 10 | (2)
Not reported ^1 | 97 | (25) | 97 | (25)
Age group
< 65 years | 255 | (67) | 280 | (73)
≥ 65 years | 127 | (33) | 103 | (27)
ECOG performance status at baseline
0 | 184 | (48) | 180 | (47)
1 | 191 | (50) | 201 | (52)
2 | 6 | (2) | 1 | (<1)
Not reported | 3 | (<1) | 3 | (<1)
MSKCC prognostic risk category
Low | 200 | (52) | 194 | (50)
Intermediate | 184 | (48) | 191 | (50)
Prior IL-2 and/or interferon
Yes | 319 | (83) | 313 | (81)
No | 65 | (17) | 72 | (19)

1 Race was not collected from the 186 patients enrolled in France due to local regulations. In 8 other patients, race was not available at the time of analysis.

Progression-free survival, defined as the time from randomization to progression or death from any cause, whichever occurred earlier, was evaluated by blinded independent radiological review using RECIST criteria. Figure 2 depicts Kaplan-Meier curves for PFS. The PFS analysis was based on a two-sided Log-Rank test stratified by MSKCC prognostic risk category and country.

Figure 2: Kaplan-Meier Curves for Progression-free Survival – TARGET (RCC)

NOTE: HR is from Cox regression model with the following covariates: MSKCC prognostic risk category and country. P-value is from two-sided Log-Rank test stratified by MSKCC prognostic risk category and country.

The median PFS for patients randomized to NEXAVAR was 167 days compared to 84 days for patients randomized to placebo. The estimated hazard ratio (immediate risk of progression or death with NEXAVAR compared to placebo) was 0.44 (95% CI: 0.35, 0.55).

A series of patient subsets were examined in exploratory univariate analyses of PFS. The subsets included age above or below 65 years, ECOG PS 0 or 1, MSKCC prognostic risk category, whether the prior therapy was for progressive metastatic disease or for an earlier disease setting and time from diagnosis of less than or greater than 1.5 years. The effect of NEXAVAR on PFS was consistent across these subsets, including patients with no prior IL-2 or interferon therapy (N=137; 65 patients receiving NEXAVAR and 72 placebo), for whom the median PFS was 172 days in the NEXAVAR arm compared to 85 days in the placebo arm.

Tumor response was determined by independent radiologic review according to RECIST criteria. Overall, of 672 patients who were evaluable for response, 7 (2%) patients in the NEXAVAR and no (0%) patients in the placebo arms had a confirmed partial response. Thus the gain in PFS primarily reflects the stable disease population.

At the time of a planned interim survival analysis, based on 220 deaths, overall survival was longer for those randomized to NEXAVAR compared with placebo with a hazard ratio of 0.72. This analysis did not meet the prespecified criteria for statistical significance. Additional analyses are planned as the survival data mature.

BAY43-9006

BAY43-9006 (NCT00101413) was a randomized discontinuation trial in patients with metastatic malignancies, including RCC. The primary endpoint was the percentage of randomized patients remaining progression-free at 24 weeks. All patients received NEXAVAR for the first 12 weeks. Radiologic assessment was repeated at week 12. Patients with <25% change in bi-dimensional tumor measurements from baseline were randomized to NEXAVAR or placebo for a further 12 weeks. Patients who were randomized to placebo were permitted to cross over to open-label NEXAVAR upon progression. Patients with tumor shrinkage ≥25% continued NEXAVAR, whereas patients with tumor growth ≥25% discontinued treatment.

A total of 202 patients with advanced RCC were enrolled into BAY43-9006, including patients who had received no prior therapy and patients with tumor histology other than clear cell carcinoma. After the initial 12 weeks of NEXAVAR, 79 patients with RCC continued on open-label NEXAVAR, and 65 patients were randomized to NEXAVAR or placebo. After an additional 12 weeks, at week 24, for the 65 randomized patients, the progression-free rate was significantly higher in patients randomized to NEXAVAR (16/32, 50%) than in patients randomized to placebo (6/33, 18%) (p=0.0077). Progression-free survival was significantly longer in the NEXAVAR arm (163 days) than in the those randomized to placebo (41 days) (p=0.0001, HR=0.29).

14.3 Differentiated Thyroid Carcinoma

The safety and effectiveness of NEXAVAR was evaluated in a multicenter, randomized (1:1), double-blind, placebo-controlled trial (DECISION; NCT00984282) conducted in 417 patients with locally recurrent or metastatic, progressive differentiated thyroid carcinoma (DTC) refractory to radioactive iodine (RAI) treatment. Randomization was stratified by age (< 60 years versus ≥ 60 years) and geographical region (North America, Europe, and Asia). All 417 subjects were included in the ITT population for the efficacy analyses

All patients were required to have actively progressing disease defined as progression within 14 months of enrollment. RAI-refractory disease was defined based on four criteria that were not mutually exclusive. All RAI treatments and diagnostic scans were to be performed under conditions of a low iodine diet and adequate TSH stimulation. Following are the RAI-refractory criteria and the proportion of patients in the study that met each one: a target lesion with no iodine uptake on RAI scan (68%); tumors with iodine uptake and progression after RAI treatment within 16 months of enrollment (12%); tumors with iodine uptake and multiple RAI treatments with the last treatment greater than 16 months prior to enrollment, and disease progression after each of two RAI treatments administered within 16 months of each other (7%); cumulative RAI dose ≥ 600 mCi administered (34%). The major efficacy outcome measure was progression-free survival (PFS) as determined by a blinded, independent radiological review using a modified Response Evaluation Criteria in Solid Tumors v. 1.0 (RECIST). RECIST was modified by inclusion of clinical progression of bone lesions based on the need for external beam radiation (4.4% of progression events). Additional efficacy outcomes measures included overall survival (OS), tumor response rate, and duration of response.

Patients were randomized to receive NEXAVAR 400 mg twice daily (n=207) or placebo (n=210). Of the 417 patients randomized, 48% were male, the median age was 63 years, 61% were 60 years or older, 60% were white, 62% had an ECOG performance status of 0, and 99% had undergone thyroidectomy. The histological diagnoses were papillary carcinoma in 57%, follicular carcinoma (including Hürthle cell) in 25%, and poorly differentiated carcinoma in 10%, and other in 8% of the study population. Metastases were present in 96% of the patients: lungs in 86%, lymph nodes in 51%, and bone in 27%. The median cumulative RAI activity administered prior to study entry was 400 mCi.

A statistically significant prolongation of PFS was demonstrated for NEXAVAR-treated patients compared to those receiving placebo (Figure 3); no statistically significant difference was seen in the final overall survival (OS) analysis (Table 12). Crossover to open label NEXAVAR occurred in 161 (77%) patients randomized to placebo after investigator-determined disease progression

Table 12: Efficacy Results from DECISION in Differentiated Thyroid Carcinoma
 | NEXAVAR N=207 | Placebo N=210
Progression-free Survival^1
Number of Deaths or Progression | 113 (55%) | 136 (65%)
Median PFS in Months (95% CI) | 10.8 (9.1, 12.9) | 5.8 (5.3, 7.8)
Hazard Ratio (95% CI) | 0.59 (0.46, 0.76)
P-value ^2 | <0.001
Overall Survival^3
Number of Deaths | 103 (49.8%) | 109 (51.9%)
Median OS in Months (95% CI) | 42.8 (34.6, 52.6) | 39.4 (32.7, 51.4)
Hazard Ratio (95% CI) | 0.92 (0.71, 1.21)
P-value^2 | 0.570
Objective Response
Number of Objective Responders ^4 | 24 (12%) | 1 (0.5%)
(95% CI) | (7.6%, 16.8%) | (0.01%, 2.7%)
Median Duration of Response in Months (95% CI) | 10.2 (7.4, 16.6) | NE
1 Independent radiological review
2 Two-sided log-rank test stratified by age (< 60 years, ≥ 60 years) and geographic region (North America, Europe, Asia)
3 Conducted after 212 events, which occurred 36 months after the primary PFS analysis.
4 All objective responses were partial responses
NR = Not Reached, CI = Confidence interval, NE = Not Estimable

Figure 3: Kaplan-Meier Curve of Progression-Free Survival in DECISION (DTC)

16 HOW SUPPLIED/STORAGE AND HANDLING

NEXAVAR is supplied in bottles of 120:

- 200 mg, round, biconvex, red film-coated tablets, debossed with the “Bayer cross” on one side and “200” on the other side. NDC 50419-488-58
- 200 mg, round, faceted, biconvex, red film-coated tablets, debossed with the “Bayer cross” on one side and “200” on the other side. NDC 50419-489-01

Store at 20°C to 25° C (68°F to 77° F); excursions permitted to 15°C to 30° C (59°F to 86° F) [see USP controlled room temperature]. Store in a dry place.

17 PATIENT COUNSELING INFORMATION

Advise the patient to read FDA-approved patient labeling (Patient Information).

Cardiovascular Events

Discuss with patients that cardiac ischemia and/or infarction and congestive heart failure, have been reported during NEXAVAR treatment, and that they should immediately report any episodes of chest pain or other symptoms of cardiac ischemia or congestive heart failure [see Warnings and Precautions (5.1)].

Bleeding

Inform patients that NEXAVAR can increase the risk of bleeding and that they should promptly report any episodes of bleeding [see Warnings and Precautions (5.2)].

Inform patients that bleeding or elevations in the International Normalized Ratio (INR) have been reported in some patients taking warfarin while on NEXAVAR and that their INR should be monitored regularly [see Warnings and Precautions (5.6)].

Hypertension

Inform patients that hypertension can develop during NEXAVAR treatment, especially during the first six weeks of therapy, and that blood pressure should be monitored regularly during treatment [see Warnings and Precautions (5.3)].

Skin Reactions

Advise patients of the possible occurrence of hand-foot skin reaction and rash during NEXAVAR treatment and appropriate countermeasures [see Warnings and Precautions (5.4)].

Gastrointestinal Perforation

Advise patients that cases of gastrointestinal perforation have been reported in patients taking NEXAVAR [see Warnings and Precautions (5.5)].

Risk of Impaired Wound Healing

Advise patients that NEXAVAR may impair wound healing. Advise patients to inform their healthcare provider of any planned surgical procedure [see Warnings and Precautions (5.7)].

QT Interval Prolongation

Inform patients with a history of prolonged QT interval that NEXAVAR can worsen the condition [see Warnings and Precautions (5.9) and Clinical Pharmacology (12.2)].

Drug-Induced Liver Injury

Inform patients that NEXAVAR can cause hepatitis which may result in hepatic failure and death. Advise patients that liver function tests should be monitored regularly during treatment and to report signs and symptoms of hepatitis [see Warnings and Precautions (5.10)].

Embryo-Fetal Toxicity

Advise females to inform their healthcare provider if they are pregnant or become pregnant. Inform female patients of the risk to a fetus and potential loss of pregnancy [see Use in Specific Populations (8.1)]. Advise females of reproductive potential to use effective contraception during treatment with NEXAVAR and for 6 months after the last dose. Advise male patients with female partners of reproductive potential or who are pregnant to use effective contraception during treatment with NEXAVAR and for 3 months after receiving the last dose of NEXAVAR [see Warnings and Precautions (5.11), Use in Specific Populations (8.1, 8.3)].

Lactation

Advise patients not to breastfeed while taking NEXAVAR and for 2 weeks after receiving the last dose of NEXAVAR [see Use in Specific Populations (8.2)].

Missed Doses

Instruct patients that if a dose of NEXAVAR is missed, the next dose should be taken at the regularly scheduled time, and not double the dose. Instruct patients to contact their healthcare provider immediately if they take too much NEXAVAR.

Patient Package Insert

Patient Information

NEXAVAR® (NEX-A-VAR)

(sorafenib)

tablets, oral

What is NEXAVAR?

NEXAVAR is a prescription medicine used to treat:

- a type of liver cancer called hepatocellular carcinoma (HCC) that cannot be removed by surgery
- a type of kidney cancer called renal cell carcinoma (RCC)
- a type of thyroid cancer called differentiated thyroid carcinoma (DTC) that can no longer be treated with radioactive iodine and is progressing

It is not known if NEXAVAR is safe and effective in children.

Do not take NEXAVAR if you:

- are allergic to sorafenib or any of the other ingredients in NEXAVAR. See the end of this leaflet for a complete list of ingredients in NEXAVAR.
- have squamous cell lung cancer and receive carboplatin and paclitaxel.

Before taking NEXAVAR, tell your healthcare provider about all of your medical conditions including if you:

- have heart problems including a condition called “congenital long QT syndrome”
- have chest pain
- have abnormal magnesium, potassium, or calcium blood levels
- have bleeding problems
- have high blood pressure
- plan to have surgery or have had a recent surgery. You should stop taking NEXAVAR at least 2 weeks before planned surgery. See “What are the possible side effects of NEXAVAR?”
- are pregnant or plan to become pregnant. NEXAVAR may harm your unborn baby. Tell your healthcare provider right away if you become pregnant during treatment with NEXAVAR.
- For females who are able to become pregnant:
- Your healthcare should do a pregnancy test before you start treatment with NEXAVAR.
- Use effective birth control (contraception) during your treatment with NEXAVAR and for 6 months after the last dose of NEXAVAR.
- For males with female partners who are able to become pregnant:
- Use effective birth control (contraception) during your treatment with NEXAVAR and for 3 months after the last dose of NEXAVAR.
- are breast feeding or plan to breastfeed. It is not known if NEXAVAR passes into your breast milk. Do not breastfeed during treatment with NEXAVAR and for 2 weeks after receiving the last dose of NEXAVAR.

Tell your healthcare provider about all the medicines you take, including prescription and over-the-counter medicines, vitamins, and herbal supplements.

Especially tell your healthcare provider if you take the medicine warfarin.

How should I take NEXAVAR?

- Take NEXAVAR exactly as your healthcare provider tells you to take it.
- Take NEXAVAR 2 times a day. Your healthcare provider may change your dose, temporarily stop treatment or completely stop treatment with NEXAVAR if you have side effects.
- Take NEXAVAR without food (at least 1 hour before or 2 hours after a meal).
- If you miss a dose of NEXAVAR, skip the missed dose, and take your next dose at your regular time. Do not double your dose of NEXAVAR.
- If you take too much NEXAVAR call your doctor or go to the nearest hospital emergency room right away.

What are the possible side effects of NEXAVAR?

NEXAVAR may cause serious side effects, including:

- decreased blood flow to the heart, heart attack and heart failure. Get emergency help right away if you get symptoms such as chest pain, shortness of breath, racing heartbeat, swelling in lower legs, feet and abdomen, feel lightheaded or faint, tiredness, nausea, vomiting, or sweat a lot.
- increased risk of bleeding. Bleeding is a common side effect of NEXAVAR that can be serious and can lead to death. Tell your healthcare provider right away if you have any signs of bleeding during treatment with NEXAVAR:

- vomiting blood or if your vomit looks like coffee-grounds
- pink or brown urine
- red or black (looks like tar) stools
- coughing up blood or blood clots

- heavier than normal menstrual cycle
- unusual vaginal bleeding
- frequent nose bleeds
- bruising

- high blood pressure. High blood pressure is a common side effect of NEXAVAR and can be serious. Your blood pressure should be checked every week during the first 6 weeks of starting NEXAVAR. Your blood pressure should be checked regularly and any high blood pressure should be treated during treatment with NEXAVAR.
- skin problems. A condition called hand-foot skin reactions and skin rash are common with NEXAVAR treatment and can be severe. NEXAVAR may also cause severe skin and mouth reactions that can be life-threatening. Tell your healthcare provider if you have any of the following symptoms:
- skin rash
- skin redness
- pain or swelling
- blistering and peeling of your skin
- blistering and peeling on the inside of your mouth
- blisters on the palms of your hand or soles of your feet
- an opening in the wall of your stomach or intestines (gastrointestinal perforation). Tell your healthcare provider right away if you get fever, nausea, vomiting or severe stomach (abdominal) pain.
- risk of wound healing problems. Wounds may not heal properly during NEXAVAR treatment. Tell your healthcare provider if you plan to have any surgery before starting or during treatment with NEXAVAR.
- You should stop taking NEXAVAR at least 10 days before planned surgery.
- Your healthcare provider should tell you when you may start taking NEXAVAR again after surgery.
- changes in the electrical activity of your heart called QT prolongation. QT prolongation can cause irregular heartbeats that can be life-threatening. Your healthcare provider may do tests during your treatment with NEXAVAR to check the levels of potassium, magnesium, and calcium in your blood, and check the electrical activity of your heart with an electrocardiogram (ECG). Tell your healthcare provider right away if you feel faint, lightheaded, dizzy or feel your heart beating irregularly or fast during your treatment with NEXAVAR.
- liver problems (drug-induced hepatitis). NEXAVAR may cause liver problems that may lead to liver failure and death. Your healthcare provider will do blood tests to check your liver function regularly during your treatment with NEXAVAR. Tell your healthcare provider right away if you develop any of the following symptoms:
- yellowing of your skin or the whites of your eyes
- dark “tea-colored” urine
- light-colored bowel movements (stools)
- worsening nausea or vomiting
- pain on the right side of your stomach area
- bleeding or bruising more easily than normal
- loss of appetite
- change in thyroid hormone levels. If you have differentiated thyroid cancer, you can have changes in your thyroid hormone levels during treatment with NEXAVAR. Your healthcare provider may need to change your dose of thyroid medicine during treatment with NEXAVAR. Your healthcare provider should check your thyroid hormone levels every month during treatment with NEXAVAR.

The most common side effects of NEXAVAR include:

- diarrhea (frequent or loose bowel movements)
- tiredness
- infection
- hair thinning or patchy hair loss
- rash

- weight loss
- loss of appetite
- nausea
- stomach-area (abdomen) pain
- low blood calcium levels in people with differentiated thyroid cancer

NEXAVAR may cause fertility problems in males. This may affect your ability to father a child. Talk to your healthcare provider if this is a concern for you.

These are not all of the possible side effects of NEXAVAR. Call your doctor for medical advice about side effects. You may report side effects to FDA at 1-800-FDA-1088.

How should I store NEXAVAR?

- Store NEXAVAR tablets at room temperature between 68° F to 77° F (20° C to 25° C).
- Store NEXAVAR tablets in a dry place.

Keep NEXAVAR and all medicines out of the reach of children.

General information about the safe and effective use of NEXAVAR

Medicines are sometimes prescribed for purposes other than those listed in a Patient Information leaflet. Do not use NEXAVAR for a condition for which it is not prescribed. Do not give NEXAVAR to other people even if they have the same symptoms you have. It may harm them. You can ask your healthcare provider or pharmacist for information about NEXAVAR that is written for health professionals.

What are the ingredients in NEXAVAR?

Active Ingredient: sorafenib tosylate

Inactive Ingredients: croscarmellose sodium, ferric oxide red, hypromellose, magnesium stearate, microcrystalline cellulose, sodium lauryl sulphate, polyethylene glycol, and titanium dioxide.

Manufactured for:
  Bayer HealthCare Pharmaceuticals Inc.
  Whippany, NJ 07981
Manufactured in Germany

© 2015 Bayer HealthCare Pharmaceuticals Inc.

For more information, go to www.NEXAVAR.com, or call 1-866-639-2827.

This Patient Information has been approved by the U.S. Food and Drug Administration. Revised 6/2020

PACKAGE/LABEL PRINCIPAL DISPLAY PANEL

Nexavar 200 mg Bottle Label

Rx Only

NDC 50419-489-01

Nexavar®
(sorafenib) tablets

Each tablet contains
200 mg
sorafenib

120 Tablets

PACKAGE/LABEL PRINCIPAL DISPLAY PANEL

Nexavar 200 mg Bottle Label

Rx Only

NDC 50419-488-58

Nexavar®
(sorafenib) tablets

Each tablet contains
200 mg
sorafenib

120 Tablets